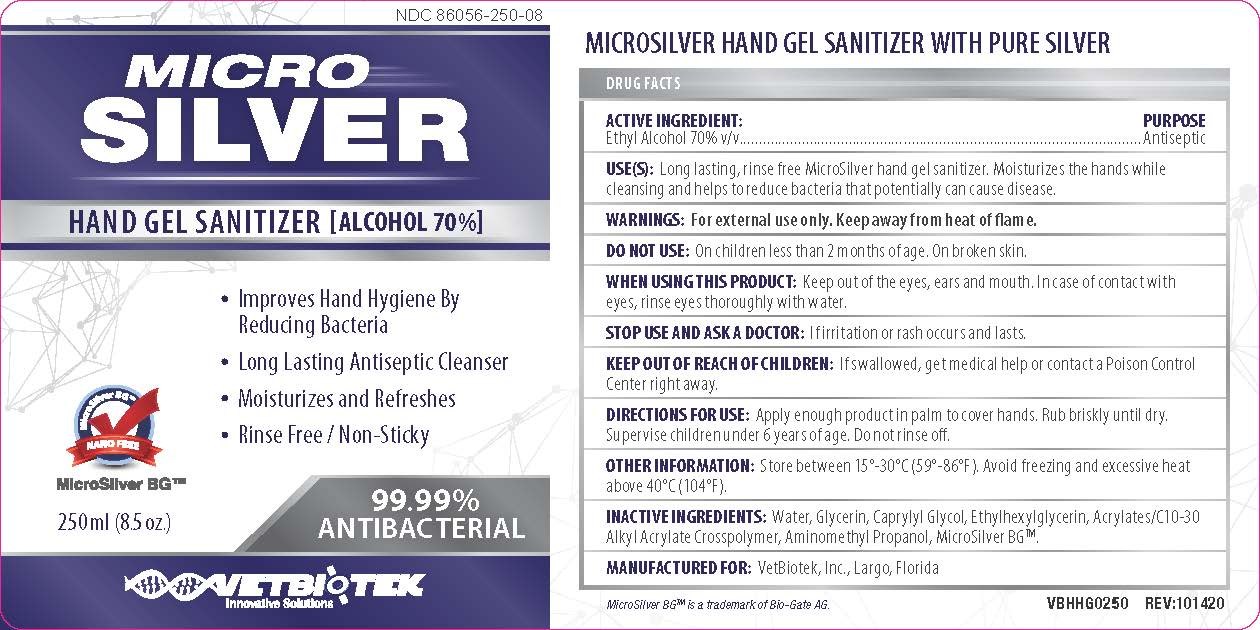 DRUG LABEL: Microsilver
NDC: 86056-250 | Form: GEL
Manufacturer: VetBiotek Inc.
Category: otc | Type: HUMAN OTC DRUG LABEL
Date: 20201014

ACTIVE INGREDIENTS: ALCOHOL 70 mL/100 mL
INACTIVE INGREDIENTS: GLYCERIN; CAPRYLYL GLYCOL; AMINOMETHYLPROPANOL; CARBOMER INTERPOLYMER TYPE A (ALLYL SUCROSE CROSSLINKED); SILVER; WATER; ETHYLHEXYLGLYCERIN

ACTIVE INGREDIENTS

Ethyl Alcohol 70% v/v

PURPOSE

Antiseptic

USE

Long lasting, rinse free MicroSilver hand gel sanitizer. Moisturizes the hands while cleansing and helps to reduce bacteria that potentially can cause disease.

WARNINGS

For external use only. Keep away from heat or flame.

DO NOT USE

On children less than 2 months of age. Avoid contact with broken skin.

WHEN USING THIS PRODUCTS

Keep out of the eyes, ears and mouth. In case of contact with eyes, rinse eyes thoroughly with water.

STOP USE AND ASK A DOCTOR

If irritation or rash appears and lasts.

KEEP OUT OF REACH OF CHILDREN

If swallowed, get medical help and contact a Poison Control Centre right away.

DIRECTIONS

Apply enough product in palm to cover hands. Rub briskly until dry. Supervise children under 6 years of age. Do not rinse off.

OTHER INFORMATION

Store between 15°-30°C (59°-86°F). Avoid freezing and excessive heat above 40°C (104°F)

INACTIVE INGREDIENTS

Water, Glycerin, Caprylyl Glycol, Ethylhexylglycerin, Acrylates/C10-30 Alkyl Acrylate Crosspolymer, Aminomethyl Propanol, Silver

PACKAGE LABEL

MICRO

SILVER

HAND GEL SANITIZER [ALCOHOL 70%]

- Improves Hand Hygiene By Reducing Bacteria
- Long Lasting Antiseptic Cleanser
- Moisturizes and Refreshes
- Rinse Free / Non-Sticky

99.99%

ANTIBACTERIAL

VETBIOTEK

Innovative Solutions